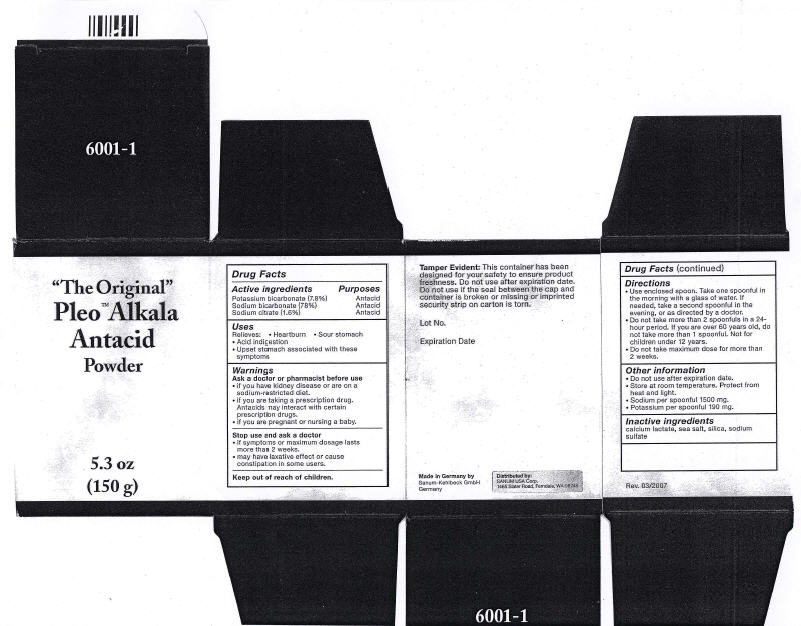 DRUG LABEL: Pleo Alkala Antacid
NDC: 60681-6001 | Form: POWDER
Manufacturer: Sanum Kehlbeck GmbH & Co. KG
Category: otc | Type: HUMAN OTC DRUG LABEL
Date: 20091016

ACTIVE INGREDIENTS: sodium bicarbonate 11.70 g/150 g; potassium bicarbonate 117 g/150 g; sodium citrate 2.4 g/150 g
INACTIVE INGREDIENTS: calcium lactate; sea salt; sodium sulfate

"The Original"
Pleo™ Alkala
Antacid
Powder

5.3 oz
(150 g)

Drug Facts

ACTIVE INGREDIENT

PURPOSE

Active Ingredients | Purposes
Potassium bicarbonate (7.8%) | Antacid
Sodium bicarbonate (78%) | Antacid
Sodium citrate (1.6%) | Antacid

Uses

Relieves:

- Heartburn
- Sour stomach
- Acid indigestion
- Upset stomach associated with these symptoms

Warnings

Ask a doctor or pharmacist before use

- if you have kidney disease or are on a sodium-restricted diet.
- if you are taking a prescription drug. Antacids may interact with certain prescription drugs.
- if you are pregnant or nursing a baby.

Stop use and ask a doctor

- if symptoms or maximum dosage lasts more than 2 weeks.
- may have laxative effect or cause constipation in some users.

Keep out of reach of children.

Tamper Evident

This container has been designed for your safety to ensure product freshness. Do not use after expiration date. Do not use if the seal between the cap and container is broken or missing or imprinted security strip on carton is torn.

Directions

- Use enclosed spoon. Take one spoonful in the morning with a glass of water. If needed, take a second spoonful in the evening, or as directed by a doctor.
- Do not take more than 2 spoonfuls in a 24-hour period. If you are over 60 years old, do not take more than 1 spoonful. Not for children under 12 years.
- Do not take maximum dose for more than 2 weeks.

Other information

- Do not use after expiration date.
- Store at room temperature. Protect from heat and light.
- Sodium per spoonful 1500 mg.
- Potassium per spoonful 190 mg.

Inactive ingredients

calcium lactate, sea salt, silica, sodium sulfate

Rev. 03/2007

Made in Germany by
Sanum-Kehlbeck GmbH
Germany

Distributed by:
SANUM USA Corp.
1465 Slater Road, Ferndale, WA 98248

PRINCIPAL DISPLAY PANEL - 150 g Carton

"The Original"
Pleo™ Alkala
Antacid
Powder

5.3 oz
(150 g)